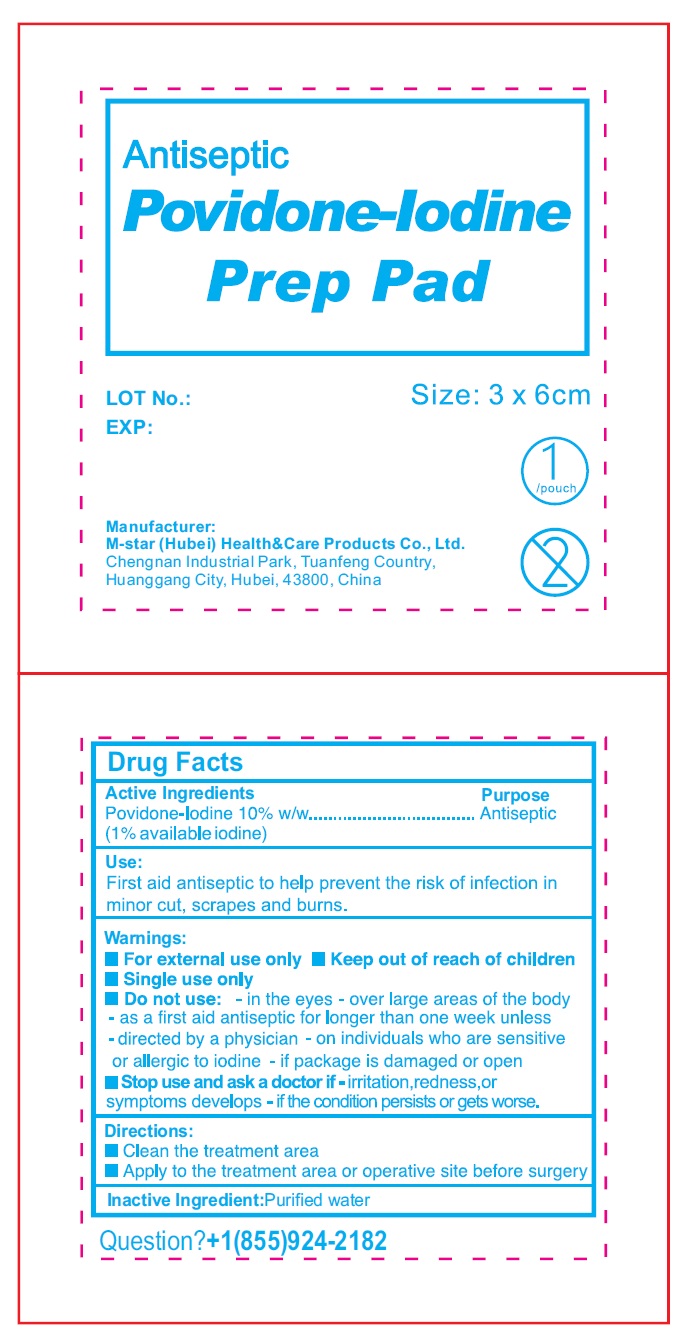 DRUG LABEL: Antiseptic Povidone Iodine Prep Pad
NDC: 84219-006 | Form: CLOTH
Manufacturer: M-star (Hubei) Health&Care Products Co., Ltd.
Category: otc | Type: HUMAN OTC DRUG LABEL
Date: 20240401

ACTIVE INGREDIENTS: POVIDONE-IODINE 100 mg/1 g
INACTIVE INGREDIENTS: WATER

Antiseptic Povidone-Iodine Prep Pad

Active Ingredients

Providone-Iodine 10% w/w (1% available iodine)

Purpose

Antiseptic

Use:

First aid antiseptic to help prevent the risk of infection in minor cut, scrapes and burns.

Warnings:

- For external use only
- Single use only

Do not use:

- in the eyes
- over large areas of the body
- as a first aid antiseptic for longer than one week unless
- directed by a physician
- on individuals who are sensitive or allergic to iodine
- if package is damaged or open

Stop use and ask a doctor if

- irritation,redness,or symptoms develops
- if the condition persists or gets worse.

Directions:

- Clean the treatment area
- Apply to the treatment area or operative site before surgery

Inactive Ingredient:

Purified water

Question?

+1(855)924-2182